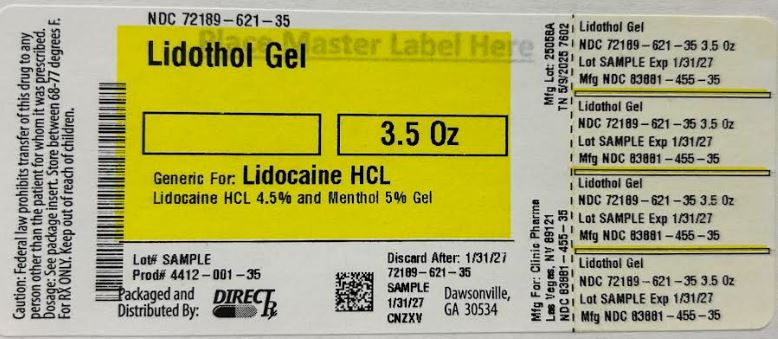 DRUG LABEL: Lidothol Gel
NDC: 72189-621 | Form: GEL
Manufacturer: Direct_Rx
Category: prescription | Type: HUMAN PRESCRIPTION DRUG LABEL
Date: 20250512

ACTIVE INGREDIENTS: LIDOCAINE HYDROCHLORIDE 4.5 g/100 g; MENTHOL 5 g/100 g
INACTIVE INGREDIENTS: ALCOHOL; XANTHAN GUM; ETHYLHEXYLGLYCERIN; ARNICA MONTANA FLOWER; PHENOXYETHANOL; WATER; SODIUM HYDROXIDE; POLYSORBATE 20; GLYCERIN; MAGNESIUM SULFATE, UNSPECIFIED FORM; BUTYLENE GLYCOL; ILEX PARAGUARIENSIS LEAF; DIMETHYL SULFONE; BOSWELLIA SERRATA RESIN OIL

Lidothol Gel

Lidothol Gel

(Lidocaine 4.5%, Menthol 5%)

Rx only

DESCRIPTION

Lidothol Gel (Lidocaine 4.5%, Menthol 5%) is comprised of a gel inside of a tube containing 4.5% Lidocaine and 5% Menthol.

Inactive ingredients: Acrylates/Cl0-30 Alkyl Acrylate Crosspolymer, Aqua (Water), Amica Montana Flower Extract, Boswellia Serrata Gum Extract, Butylene Glycol, Dimethyl Sulfone (MSM), Ethylhexylglycerin, Glycerin, llex Paraguariensis Leaf Extract, Magnesium Sulfate, Phenoxyethanol, Polysorbate 20, SD Alcohol 40-B, Sodium Hydroxide, Xanthan Gum

CLINICAL PHARMACOLOGY

Pharmacodynamics

Lidocaine is an amide-type local anesthetic agent. The penetration of lidocaine into intact skin after application of Lidothol Gel is sufficient to produce annalgesic effect, but less than the amount necessary to produce a complete sensory block.

Menthol is a covalent organic compound made synthetically or obtained from peppermint or other mint oils. Menthol induces a cooling sensation on the skin upon topical application by stimulating the cold-sensitive receptors expressed on the skin, without actually causing a drop in the skin temperature.

Pharmacokinetics

Absorption

The amount of lidocaine systemically absorbed from Lidothol Gel is directly related to both the duration of application and the surface area over which it is applied.

Menthol occurs in numerous over-the-counter products. Although extensively used, there have been no estimates of human exposure following administration via dermal application.

Distribution

At concentrations produced by application of Lidothol Gel, approximately 70% of the lidocaine dose is reported to be bound to plasma proteins, primarily alpha-1-acid glycoprotein. At higher plasma concentrations (1 to 4 mcg/mL of free base), the plasma protein binding of lidocaine is concentration dependent.

Metabolism

It is not known if Lidothol Gel is metabolized in the skin.

Excretion

Lidocaine and its metabolites are excreted by the kidneys. Less than 10% of lidocaine is excreted unchanged. The half-life of lidocaine elimination from the plasma following IV administration is 81 to 149 minutes (mean 107 ± 22 SD, n = 15). The systemic clearance is 0.33 to 0.90 L/min (mean 0.64 ± 2 max max 0.18 SD, n = 15).

INDICATIONS AND USAGE

Lidothol Gel is indicated for relief of pain associated with arthritis, backache, cramps, discomfort, neckache, soreness, sprains, strains. It should be applied only to intact skin.

CONTRAINDICATIONS

Lidothol Gel is contraindicated in patients with a known history of sensitivity to local anesthetics of the amide type, or to any other component of the product.

WARNINGS

Medicines intended to be applied to the skin should not be swallowed.

Lidothol Gel is flammable. Keep away from open flame.

You should never heat, microwave, or add the medicine to hot water.

Risk of Methemoglobinemia

Cases of methemoglobinemia have been reported in association with lidocaine use. Although all patients are at risk for methemoglobinemia, patients with glucose-6-phosphate dehydrogenase deficiency, congenital or idiopathic methemoglobinemia, cardiac or pulmonary compromise, infants under 6 months of age, and concurrent exposure to oxidizing agents or their metabolites are more susceptible to developing the condition. If lidocaine must be used in these patients, close monitoring for symptoms and signs of methemoglobinemia is recommended. Signs of methemoglobinemia may occur immediately or may be delayed some hours after exposure, and are characterized by a cyanotic skin discoloration and/or abnormal coloration of the blood.

Methemoglobin levels may continue to rise; therefore, immediate treatment is required to avert more

serious central nervous system and cardiovascular adverse effects, including seizures, coma,

arrhythmias, and death.

Excessive Dosing

Excessive dosing by applying Lidothol Gel to larger areas could result in increased absorption of lidocaine and high blood concentrations, leading to serious adverse effects (see ADVERSE REACTIONS, Systemic Reactions). Lidocaine toxicity could be expected at lidocaine blood concentrations above 5 mcg/mL. The blood concentration of lidocaine is determined by the rate of systemic absorption and elimination. Longer duration of application of more than the recommended number of doses, smaller patients, or impaired elimination may all contribute to increased blood concentration of lidocaine.

PRECAUTIONS

General

Hepatic Disease

Patients with severe hepatic disease are at greater risk of developing toxic blood concentrations of

Lidocaine and menthol, because of their inability to metabolize lidocaine and menthol normally.

Allergic Reactions

Patients allergic to para-aminobenzoic acid derivatives (procaine, tetracaine, benzocaine, etc.) have not

shown cross sensitivity to lidocaine. However, Lidothol Gel should be used with caution in patients

with a history of drug sensitivities, especially if the etiologic agent is uncertain.

Although rare, get emergency medical help if you have signs of an allergic reaction from oral or topical application of menthol: hives, difficulty breathing, or swelling of your face, lips, tongue, or throat.

Non-intact Skin

Application to broken or inflamed skin, although not tested, may result in higher blood concentrations of lidocaine and menthol from increased absorption. Lidothol Gel is only recommended for use on intact skin.

External Heat Sources

Placement of external heat sources, such as heating pads or electric blankets, over Lidothol Gel

is not recommended as this has not been evaluated and may increase plasma lidocaine levels.

Eye Exposure

The contact of Lidothol Gel with eyes, although not studied, should be avoided based on the findings of

severe eye irritation with the use of similar products in animals. If eye contact occurs, immediately

wash out the eye with water or saline and protect the eye until sensation returns.

Information for Patients

Methemoglobinemia

Inform patients that use of local anesthetics may cause methemoglobinemia, a serious condition that must be treated promptly. Advise patients or caregivers to stop use and seek immediate medical attention if they or someone in their care experience the following signs or symptoms: pale, gray, or blue colored skin (cyanosis); headache; rapid heart rate; shortness of breath; lightheadedness; or fatigue.

Drug Interactions

Antiarrhythmic Drugs

Lidothol Gel should be used with caution in patients receiving Class I antiarrhythmic drugs (such as

tocainide and mexiletine) since the toxic effects are additive and potentially synergistic.

Local Anesthetics

When Lidothol Gel is used concomitantly with other products containing local anesthetic agents, the

amount absorbed from all formulations must be considered.

Drugs That May Cause Methemoglobinemia When Used with Lidothol Gel

Patients who are administered local anesthetics are at increased risk of developing methemoglobinemia

when concurrently exposed to the following drugs, which could include other local anesthetics:

Examples of Drugs Associated with Methemoglobinemia:

Class Examples

Nitrates/Nitrites nitric oxide, nitroglycerin, nitroprusside, nitrous oxide

Local anesthetics

articaine, benzocaine, bupivacaine, lidocaine, mepivacaine, prilocaine, procaine, ropivacaine, tetracaine

Antineoplastic agents cyclophosphamide, flutamide, hydroxyurea, ifosfamide, rasburicase, Antibiotics dapsone, nitrofurantoin, para-aminosalicylic acid, sulfonamides, Antimalarials chloroquine, primaquine Anticonvulsants Phenobarbital, phenytoin, sodium valproate, Other drugs acetaminophen, metoclopramide, quinine, sulfasalazine Carcinogenesis, Mutagenesis

Impairment of Fertility

The effect of Lidothol Gel on fertility has not been studied.

Pregnancy

Teratogenic Effects

Pregnancy Category B.

Lidothol Gel has not been studied in pregnancy.

Labor and Delivery

Lidothol Gel has not been studied in labor and delivery.

Nursing Mothers

Lidothol Gel has not been studied in nursing mothers.

Pediatric Use

Safety and effectiveness in pediatric patients have not been established.

Application Site Reactions

During or immediately after treatment with Lidothol Gel, the skin at the site of application may develop blisters, bruising, burning sensation, depigmentation, dermatitis, discoloration, edema, erythema, exfoliation, irritation, papules, petechia, pruritus, vesicles, or may be the locus of abnormal sensation. These reactions are generally mild and transient, resolving spontaneously within a few minutes to hours.

Other Adverse Events

Due to the nature and limitation of spontaneous reports in post marketing surveillance, causality has not

been established for additional reported adverse events including:

Asthenia, confusion, disorientation, dizziness, headache, hyperesthesia, hypoesthesia, lightheadedness,

metallic taste, nausea, nervousness, pain exacerbated, paresthesia, somnolence, taste alteration,

vomiting, visual disturbances such as blurred vision, flushing, tinnitus, and tremor.

Systemic (Dose-Related) Reactions

Systemic adverse reactions following appropriate use of Lidothol Gel are unlikely, due to the small

dose absorbed (see CLINICAL PHARMACOLOGY, Pharmacokinetics). Systemic adverse effects of

lidocaine is similar in nature to those observed with other amide local anesthetic agents, including

CNS excitation and/or depression (light headedness, nervousness, apprehension, euphoria, confusion,

dizziness, drowsiness, tinnitus, blurred or double vision, vomiting, sensations of heat, cold or numbness,

twitching, tremors, convulsions, unconsciousness, respiratory depression and arrest). Excitatory CNS

reactions may be brief or not occur at all, in which case the first manifestation may be drowsiness

merging into unconsciousness. Cardiovascular manifestations may include bradycardia, hypotension and

cardiovascular collapse leading to arrest.

Sensitivity reactions associated with the use of mentholated products have been reported. Use of mentholated nasal drops in infants has evidently caused isolated cases of spasm of the larynx, and a few cases of nervous or digestive system disturbance have been associated with excessive inhalation or oral exposure to menthol

OVERDOSAGE

Lidocaine overdose from cutaneous absorption is rare but could occur. If there is any suspicion of

lidocaine overdose (see ADVERSE REACTIONS, Systemic Reactions), drug blood concentration

should be checked. The management of overdose includes close monitoring, supportive care, and

symptomatic treatment. Dialysis is of negligible value in the treatment of acute overdose with lidocaine.

In the absence of massive topical overdose or oral ingestion, evaluation of symptoms of toxicity should

include consideration of other etiologies for the clinical effects, or overdosage from other sources of

lidocaine or other local anesthetics.

DOSAGE AND ADMINISTRATION

Apply Lidothol Gel to intact skin to cover the most painful area. Clean and dry the affected area. Apply product directly to your skin, up to 4 times daily. Clothing may be worn over the area of application.

If irritation or a burning sensation occurs during application, wash the product off your skin and do not reapply until the irritation subsides.

When Lidothol Gel is used concomitantly with other products containing local anesthetic agents, the

amount absorbed from all formulations must be considered.

DISPOSAL AND WASTE HANDLING

Hands should be washed after the handling of Lidothol Gel, and eye contact with Lidothol Gel should

be avoided. Store in a cool, dry place with lid tightly closed.

Lidothol Gel should be kept out of the reach of children.

HOW SUPPLIED

Lidothol Gel is available as the following:

1 tube, 3.5oz

NDC 72189-621-35

STORAGE AND HANDLING

Store at 25°C (77°F); excursions permitted to 15°-30°C (59°-86°F). [See USP Controlled Room Temperature].

For more information, contact Clinic Pharma. Info@Clinicpharma.com

Manufactured for:

Clinic Pharma

Las Vegas, NV 89121

Printed in the U.S.A.

PATIENT INFORMATION

[Package Insert (1)]

[Package Insert (2)]